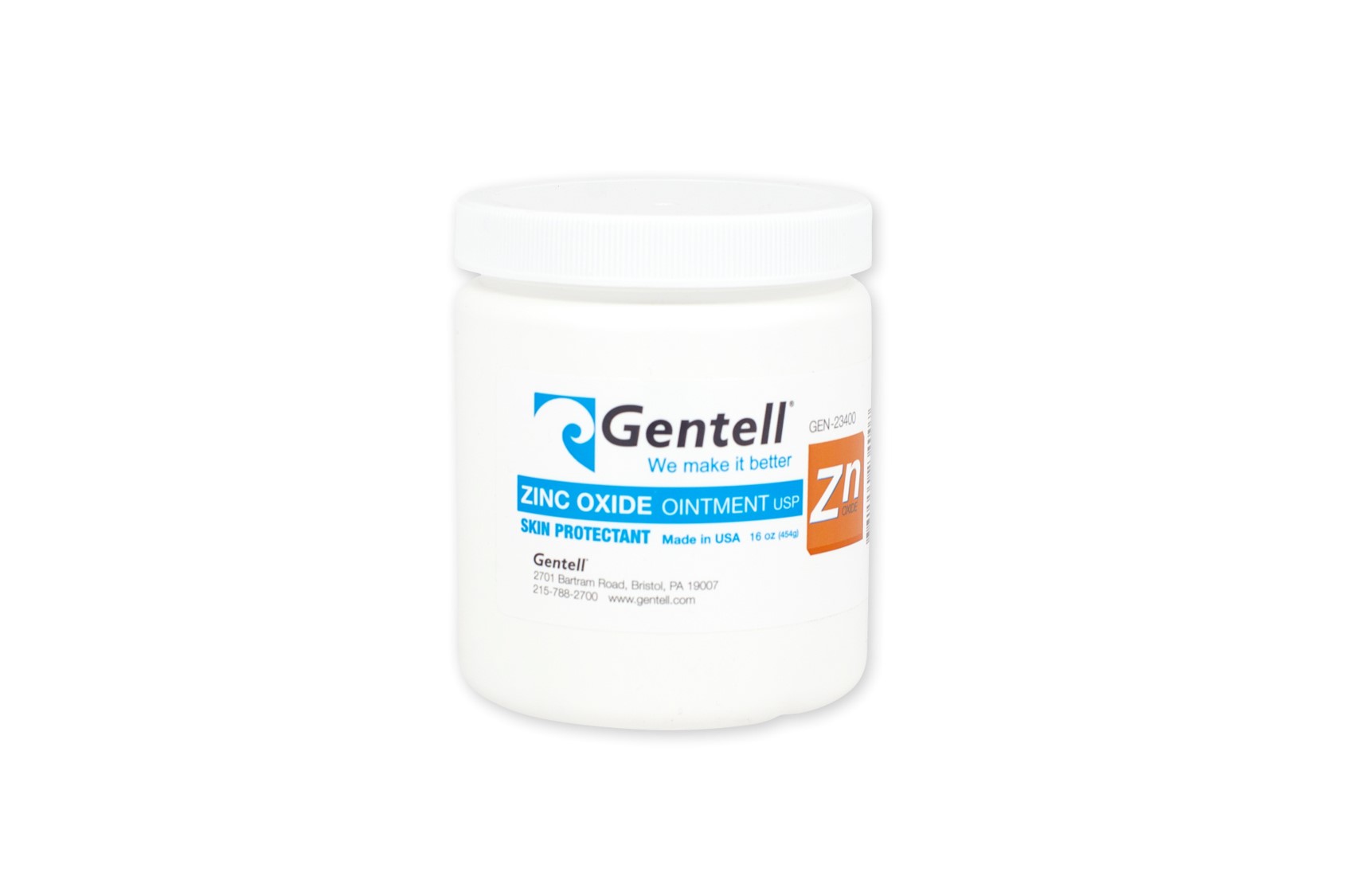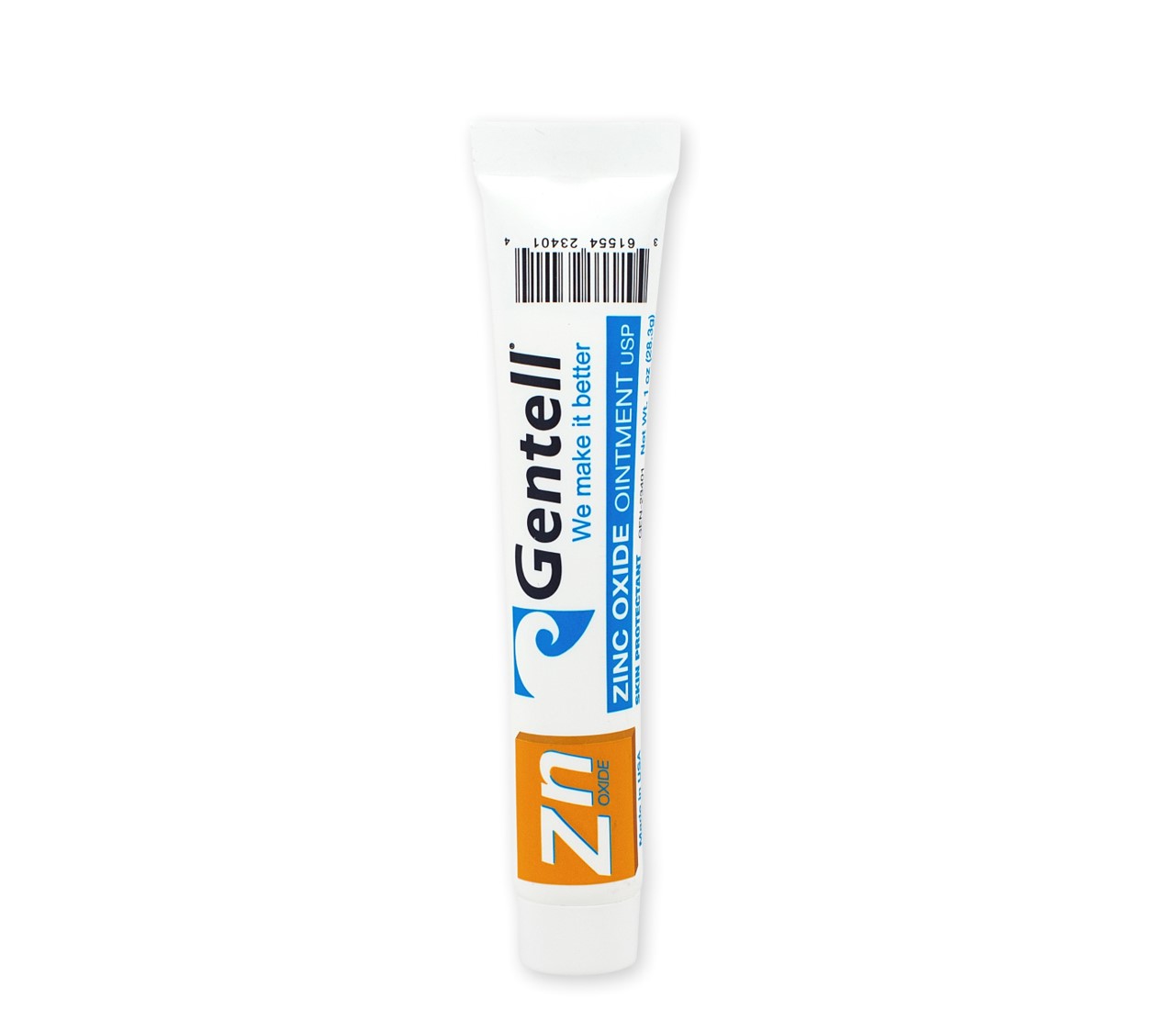 DRUG LABEL: Zinc Oxide
NDC: 61554-234 | Form: CREAM
Manufacturer: Gentell, Inc,.
Category: otc | Type: HUMAN OTC DRUG LABEL
Date: 20170322

ACTIVE INGREDIENTS: ZINC OXIDE 0.2 kg/1 kg
INACTIVE INGREDIENTS: LIGHT MINERAL OIL

Warnings

For external use only.• Avoid contact with eyes.•

Stop use & ask a doctor if condition worsens or does not improve

within 7 days.• Keep out of reach of children.•

If swallowed, get medical help or contact a Poison Control Center right away.

Uses

Helps treat & prevent diaper rash.

Protects chafed skin assoicated with diaper rash & helps

protect from wetness. Effective for treating poison ivy,

poison oak & sumac.

Inactive Ingredients

Light Mineral Oil & White Petrolatum

Active Ingredients (In each gram)

Zinc Oxide 20% Skin Protectant

Directions

Gently cleanse affected area and allow to dry before application.

Apply ointment liberally & as often as necessary.

For diaper rash, chage wet and soiled diapers promptly.

Use with each diaper change, especially when exposure to wet

diapers may be prolonged.

Other Information

Lot Number & Expiration Date; see bottom of container.

Store at controlled room temperature (59ºF - 86ºF).

KEEP OUT OF REACH OF CHILDREN

For external use only.• Avoid contact with eyes.•

Stop use & ask a doctor if condition worsens or does not improve

within 7 days.• Keep out of reach of children.•

If swallowed, get medical help or contact a Poison Control Center right away.

PURPOSE

Helps, treats and prevents diaper rash. Protects chafed skin associaed with diaper rash & helps protect from wetness.

Effective in treating poison ivy, poison oak and sumac.